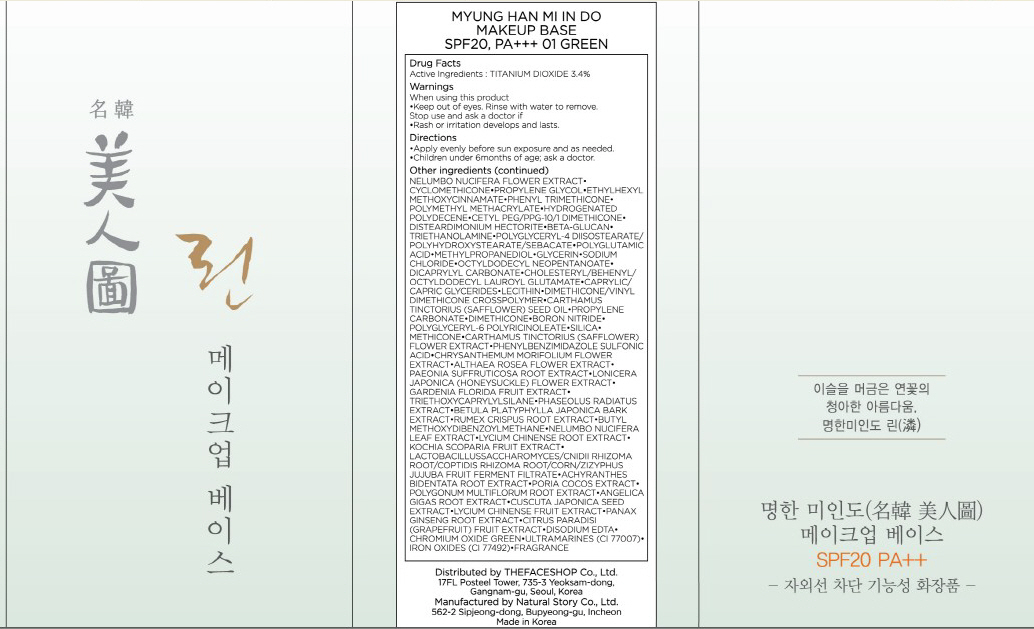 DRUG LABEL: MYUNG HAN MI IN DO MAKEUP BASE
NDC: 51523-015 | Form: CREAM
Manufacturer: THEFACESHOP CO., LTD.
Category: otc | Type: HUMAN OTC DRUG LABEL
Date: 20100714

ACTIVE INGREDIENTS: TITANIUM DIOXIDE 1.19 mL/35 mL

Drug Facts

Active Ingredient: TITANIUM DIOXIDE

Inactive Ingredients:
NELUMBO NUCIFERA FLOWER EXTRACT, CYCLOMETHICONE, PROPYLENE GLYCOL, ETHYLHEXYL METHOXYCINNAMATE, PHENYL TRIMETHICONE, POLYMETHYL METHACRYLATE, HYDROGENATED POLYDECENE, CETYL PEG/PPG-10/1 DIMETHICONE, DISTEARDIMONIUM HECTORITE, BETA-GLUCAN, TRIETHANOLAMINE, POLYGLYCERYL-4 DIISOSTEARATE/POLYHYDROXYSTEARATE/SEBACATE, POLYGLUTAMIC ACID, METHYLPROPANEDIOL, GLYCERIN, SODIUM CHLORIDE, OCTYLDODECYL NEOPENTANOATE, DICAPRYLYL CARBONATE, CHOLESTERYL/BEHENYL/OCTYLDODECYL LAUROYL GLUTAMATE, CAPRYLIC/CAPRIC GLYCERIDES, LECITHIN, DIMETHICONE/VINYL DIMETHICONE CROSSPOLYMER, CARTHAMUS TINCTORIUS (SAFFLOWER) SEED OIL, PROPYLENE CARBONATE, DIMETHICONE, BORON NITRIDE, POLYGLYCERYL-6 POLYRICINOLEATE, SILICA, METHICONE, CARTHAMUS TINCTORIUS (SAFFLOWER) FLOWER EXTRACT, PHENYLBENZIMIDAZOLE SULFONIC ACID, CHRYSANTHEMUM MORIFOLIUM FLOWER EXTRACT, ALTHAEA ROSEA FLOWER EXTRACT, PAEONIA SUFFRUTICOSA ROOT EXTRACT, LONICERA JAPONICA (HONEYSUCKLE) FLOWER EXTRACT, GARDENIA FLORIDA FRUIT EXTRACT, TRIETHOXYCAPRYLYLSILANE, PHASEOLUS RADIATUS EXTRACT, BETULA PLATYPHYLLA JAPONICA BARK EXTRACT, RUMEX CRISPUS ROOT EXTRACT,
BUTYL METHOXYDIBENZOYLMETHANE, NELUMBO NUCIFERA LEAF EXTRACT, LYCIUM CHINENSE ROOT EXTRACT, KOCHIA SCOPARIA FRUIT EXTRACT, LACTOBACILLUSSACCHAROMYCES/CNIDII RHIZOMA ROOT/COPTIDIS RHIZOMA ROOT/CORN/ZIZYPHUS JUJUBA FRUIT FERMENT FILTRATE, ACHYRANTHES BIDENTATA ROOT EXTRACT, PORIA COCOS EXTRACT, POLYGONUM MULTIFLORUM ROOT EXTRACT, ANGELICA GIGAS ROOT EXTRACT, CUSCUTA JAPONICA SEED EXTRACT,
LYCIUM CHINENSE FRUIT EXTRACT, PANAX GINSENG ROOT EXTRACT, CITRUS PARADISI (GRAPEFRUIT) FRUIT EXTRACT, DISODIUM EDTA, CHROMIUM OXIDE GREEN,
ULTRAMARINES(CI 77007), IRON OXIDES(CI 77492), FRAGRANCE

Warnings:
When using this product
Keep out of eyes. Rinse with water to remove.
Stop use and ask a doctor if
Rash or irritation develops and lasts.
Directions:
Apply evenly before sun exposure and as needed.
Children under 6months of age; ask a doctor.